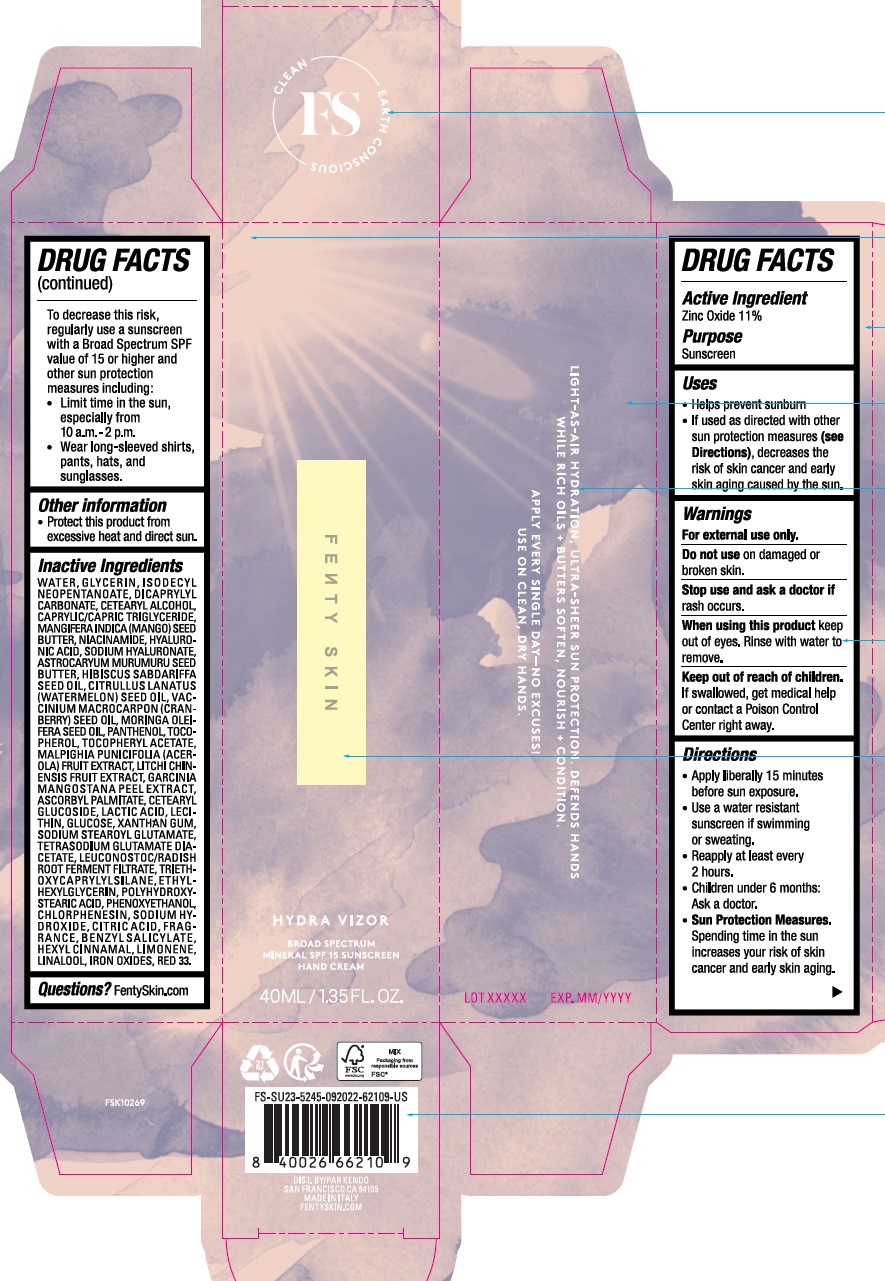 DRUG LABEL: FENTY SKIN HYDRA VIZOR BROAD SPECTRUM MINERAL SPF 15 SUNSCREEN HAND
NDC: 71499-103 | Form: CREAM
Manufacturer: KENDO HOLDINGS INC
Category: otc | Type: HUMAN OTC DRUG LABEL
Date: 20250930

ACTIVE INGREDIENTS: ZINC OXIDE 11 g/100 mL
INACTIVE INGREDIENTS: FERROUS OXIDE; WATER; GLYCERIN; DICAPRYLYL CARBONATE; CETOSTEARYL ALCOHOL; MEDIUM-CHAIN TRIGLYCERIDES; MANGIFERA INDICA SEED BUTTER; NIACINAMIDE; HYALURONIC ACID; HYALURONATE SODIUM; PHENOXYETHANOL; ASTROCARYUM MURUMURU SEED BUTTER; HIBISCUS SABDARIFFA SEED OIL; WATERMELON SEED OIL; CRANBERRY SEED OIL; MORINGA OLEIFERA SEED OIL; PANTHENOL; TOCOPHEROL; .ALPHA.-TOCOPHEROL ACETATE; MALPIGHIA GLABRA FRUIT; LITCHI FRUIT; GARCINIA MANGOSTANA FRUIT RIND; ASCORBYL PALMITATE; CETEARYL GLUCOSIDE; LACTIC ACID, DL-; LECITHIN, SOYBEAN; ANHYDROUS DEXTROSE; XANTHAN GUM; SODIUM STEAROYL GLUTAMATE; TETRASODIUM GLUTAMATE DIACETATE; LEUCONOSTOC/RADISH ROOT FERMENT FILTRATE; TRIETHOXYCAPRYLYLSILANE; D&C RED NO. 33; ETHYLHEXYLGLYCERIN; POLYHYDROXYSTEARIC ACID (2300 MW); CHLORPHENESIN; SODIUM HYDROXIDE; CITRIC ACID MONOHYDRATE; LIMONENE, (+)-; LINALOOL, (+/-)-; BENZYL SALICYLATE; ISODECYL NEOPENTANOATE

KENDO - FENTY SKIN HYDRA VIZOR BROAD SPECTRUM MINERAL SPF 15 SUNSCREEN HAND CREAM (71499-103)

ACTIVE INGREDIENTS

ZINC OXIDE 11%

PURPOSE

SUNSCREEN

USES

- HELPS PREVENT SUNBURN
- IF USED AS DIRECTED WITH OTHER SUN PROTECTION MEASURES (SEE DIRECTIONS), DECREASES THE RISK OF SKIN CANCER AND EARLY SKIN AGING CAUSED BY THE SUN.

WARNINGS

FOR EXTERNAL USE ONLY.

DO NOT USE ON DAMAGED OR BROKEN SKIN.

STOP USE AND ASK A DOCTOR IF RASH OCCURS.

WHEN USING THIS PRODUCT KEEP OUT OF EYES. RINSE WITH WATER TO REMOVE.

KEEP OUT OF REACH OF CHILDREN. IF SWALLOWED, GET MEDICAL HELP OR CONTACT A POISON CONTROL CENTER RIGHT AWAY.

DIRECTIONS

- APPLY LIBERALLY 15 MINUTES BEFORE SUN EXPOSURE.
- USE A WATER RESISTANT SUNSCREEN IF SWIMMING OR SWEATING.
- REAPPLY AT LEAST EVERY 2 HOURS.
- CHILDREN UNDER 6 MONTHS: ASK A DOCTOR.
- SUN PROTECTION MEASURES. SPENDING TIME IN THE SUN INCREASES YOUR RISK OF SKIN CANCER AND EARLY SKIN AGING. TO DECREASE THIS RISK, REGULARLY USE A SUNCREEN WITH A BROAD SPECTRUM SPF VALUE OF 15 OR HIGHER AND OTHER SUN PROTECTION MEASURES INCLUDING:
- LIMIT TIME IN THE SUN, ESPECIALLY FROM 10 A.M. - 2 P.M.
- WEAR LONG=SLEEVED SHIRTS, PANTS, HATS, AND SUNGLASSES.

OTHER INFORMATION

PROTECT THIS PRODUCT FROM EXCESSIVE HEAT AND DIRECT SUN.

INACTIVE INGREDIENTS

WATER, GLYCERIN, ISODECYL NEOPENTANOATE, DICAPRYLYL CARBONATE, CESTEARYL ALCOHOL, CAPRYLIC/CAPRIC TRIGLYCERIDES, MANGIFERA INDICA (MANGO) SEED BUTTER, NIACINAMIDE, HYALURONIC ACID, SODIUM HYALURONATE, ASTROCARYUM MURUMURU SEED BUTTER, HIBISCUS SABDARIFFA SEED OIL, CITRULLUS LANATUS (WATERMELON) SEED OIL, VACCINIUM MACROCARPON (CRANBERRY) SEED OIL, MORINGA OLEIFERA SEED OIL, PANTHENOL, TOCOPHEROL, TOCOPHEROL ACETATE, MALPIGHIA PUNICIFOLIA (ACEROLA) FRUIT EXTRACT, LITCHI CHINENSIS FRUIT EXTRACT, GARCINIA MANGOSTANA PEEL EXTRACT, ASCORBYL PALMITATE, CETEARYL GLUCOSIDE, LACTIC ACID, LECITHIN, GLUCOSE, XANTHAN GUM, SODIUM STEAROYL GLUTAMATE, TETRASODIUM GLUTAMATE DIACETATE, LEUCONOSTOC/RADISH ROOT FERMENT FILTRATE, TRIETHOXYCAPRYLYLSILANE, ETHYLHEXYLGLYCERIN, POLYHYDROXYSTEARIC ACID, PHENOXYETHANOL, CHLORPHENESIN, SODIUM HYDROXIDE, CITRIC ACID, FRAGRANCE, BENZYL SALICYLATE, HEXYL CINNAMA, LIMONENE, LINALOOL, IRON OXIDES, RED 33.

QUESTIONS?

FENTYSKIN.COM